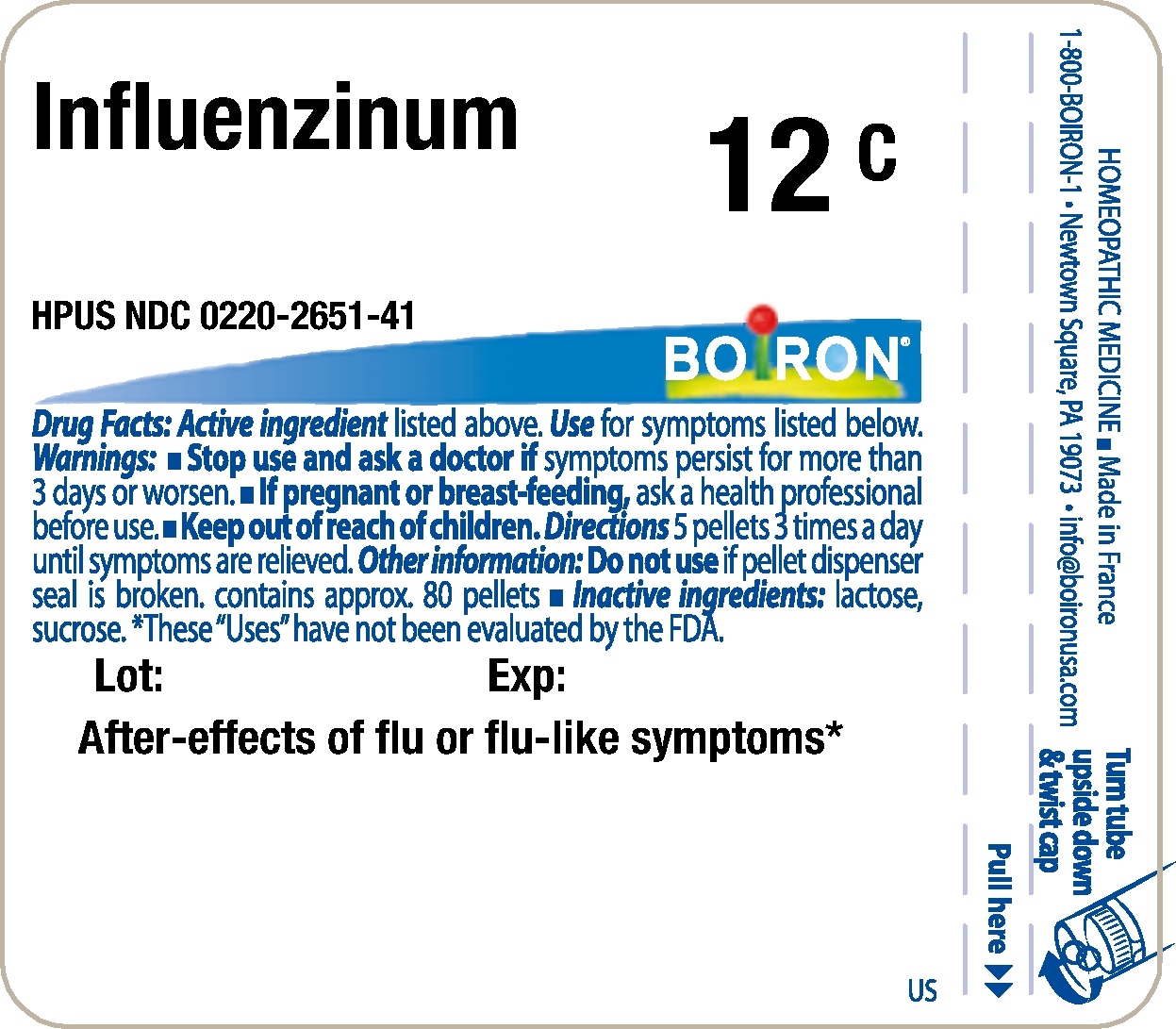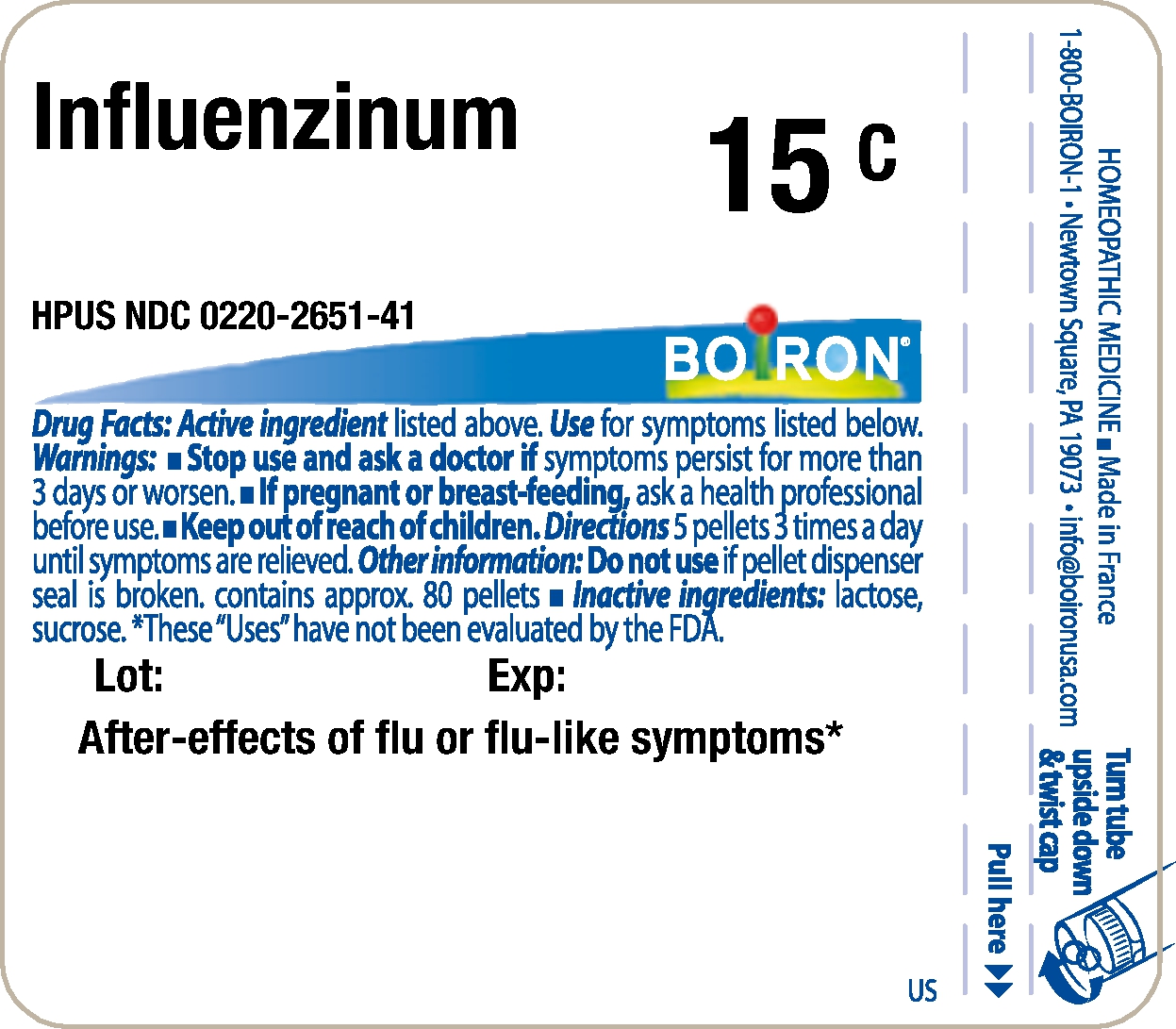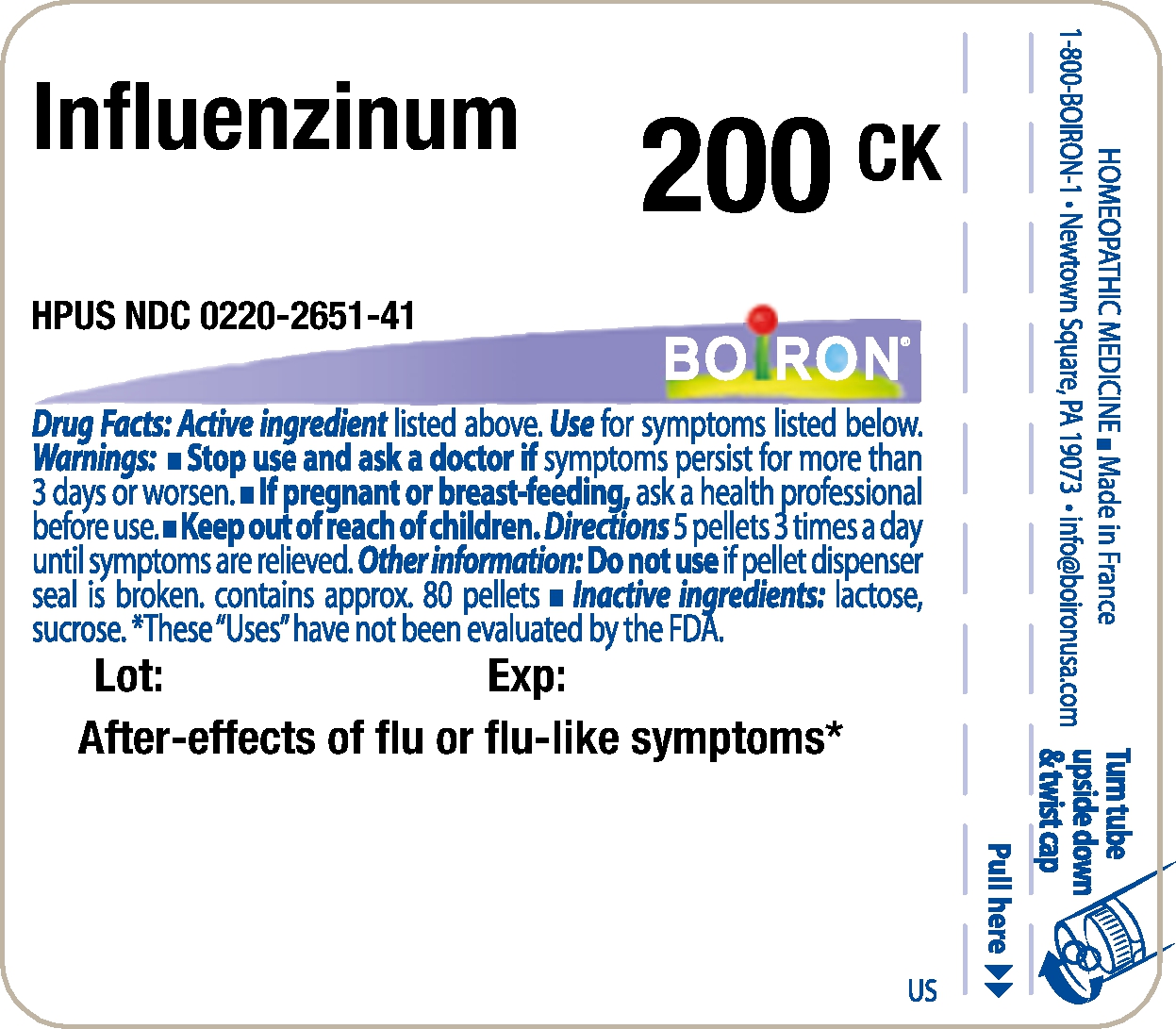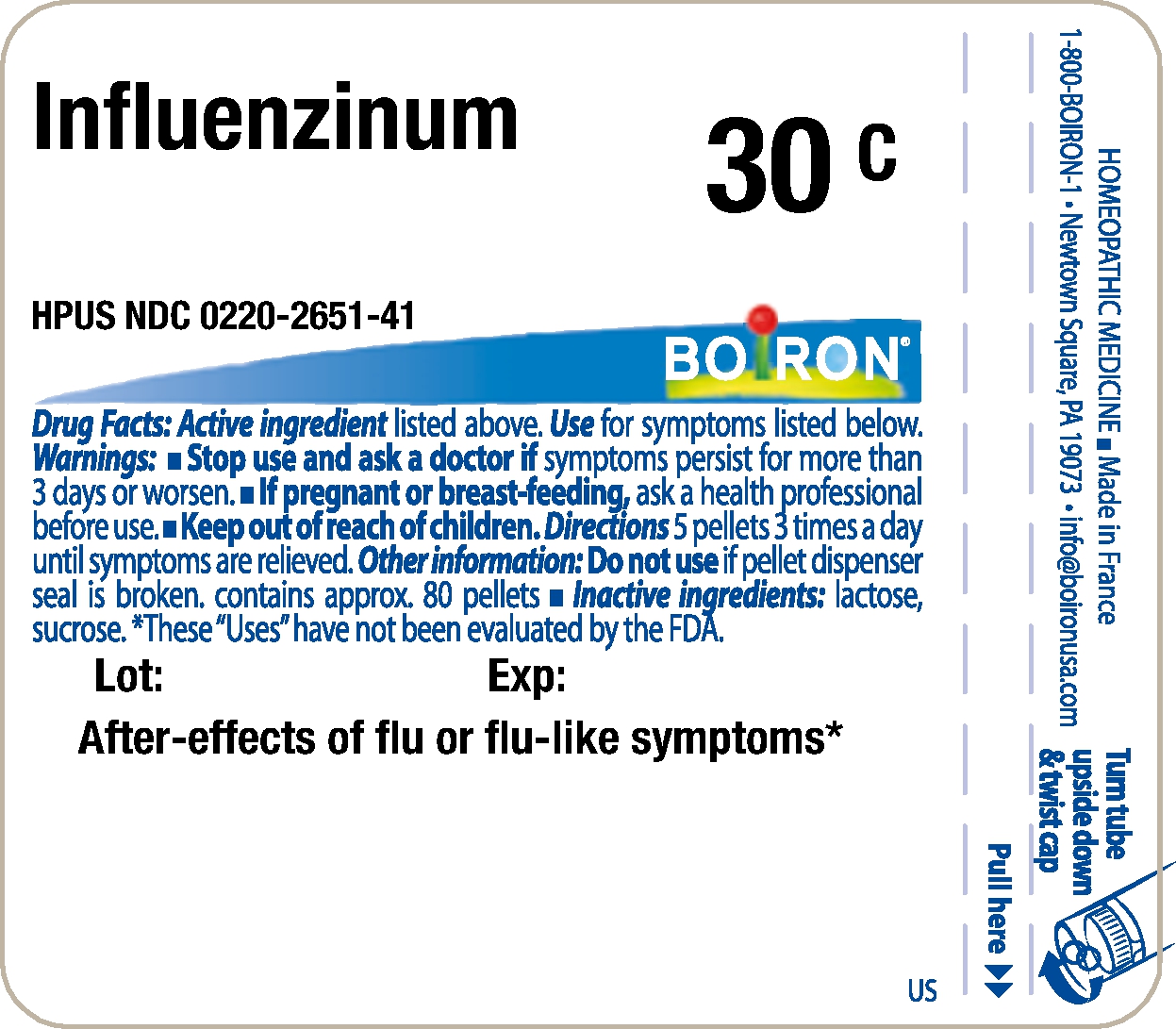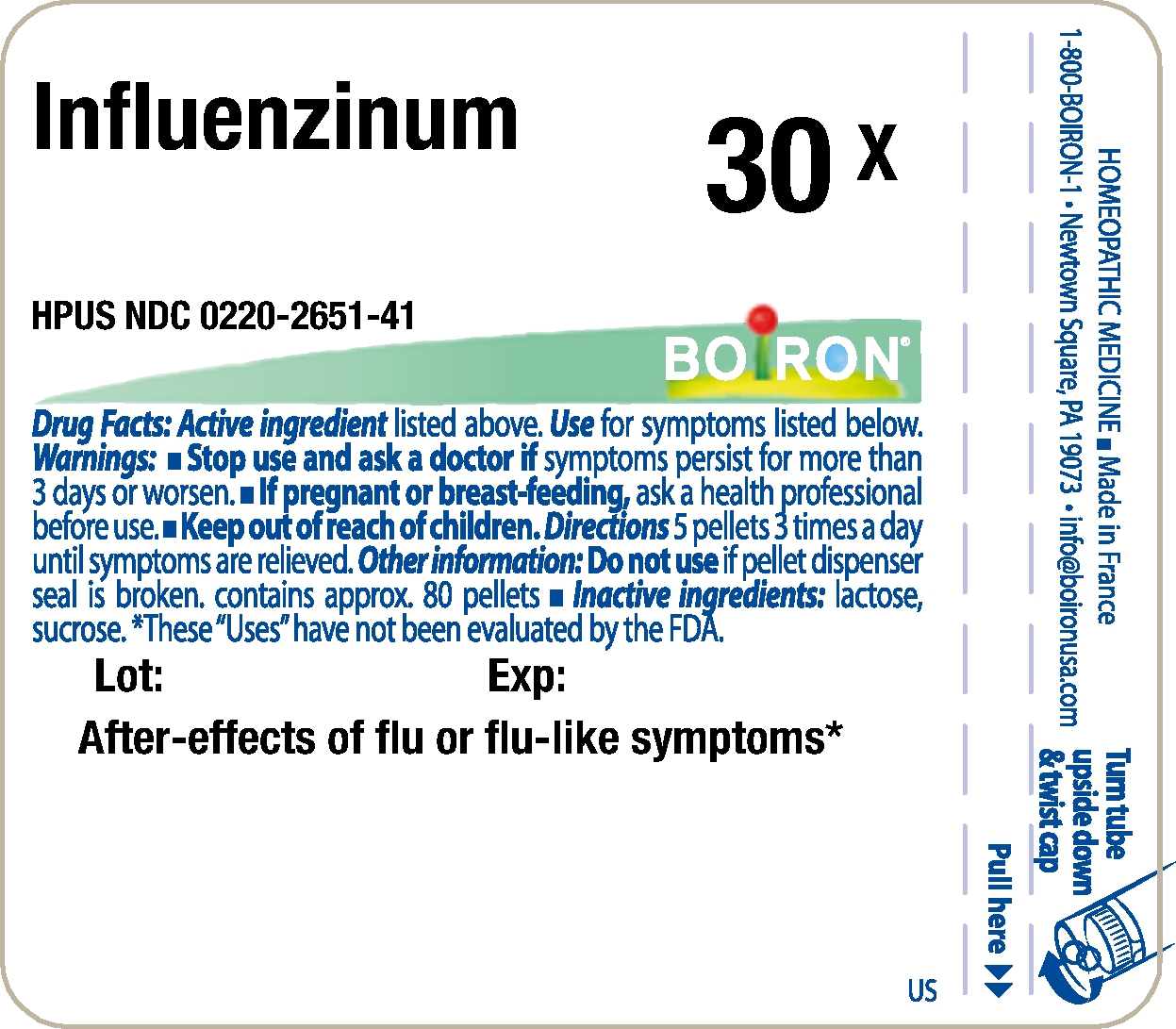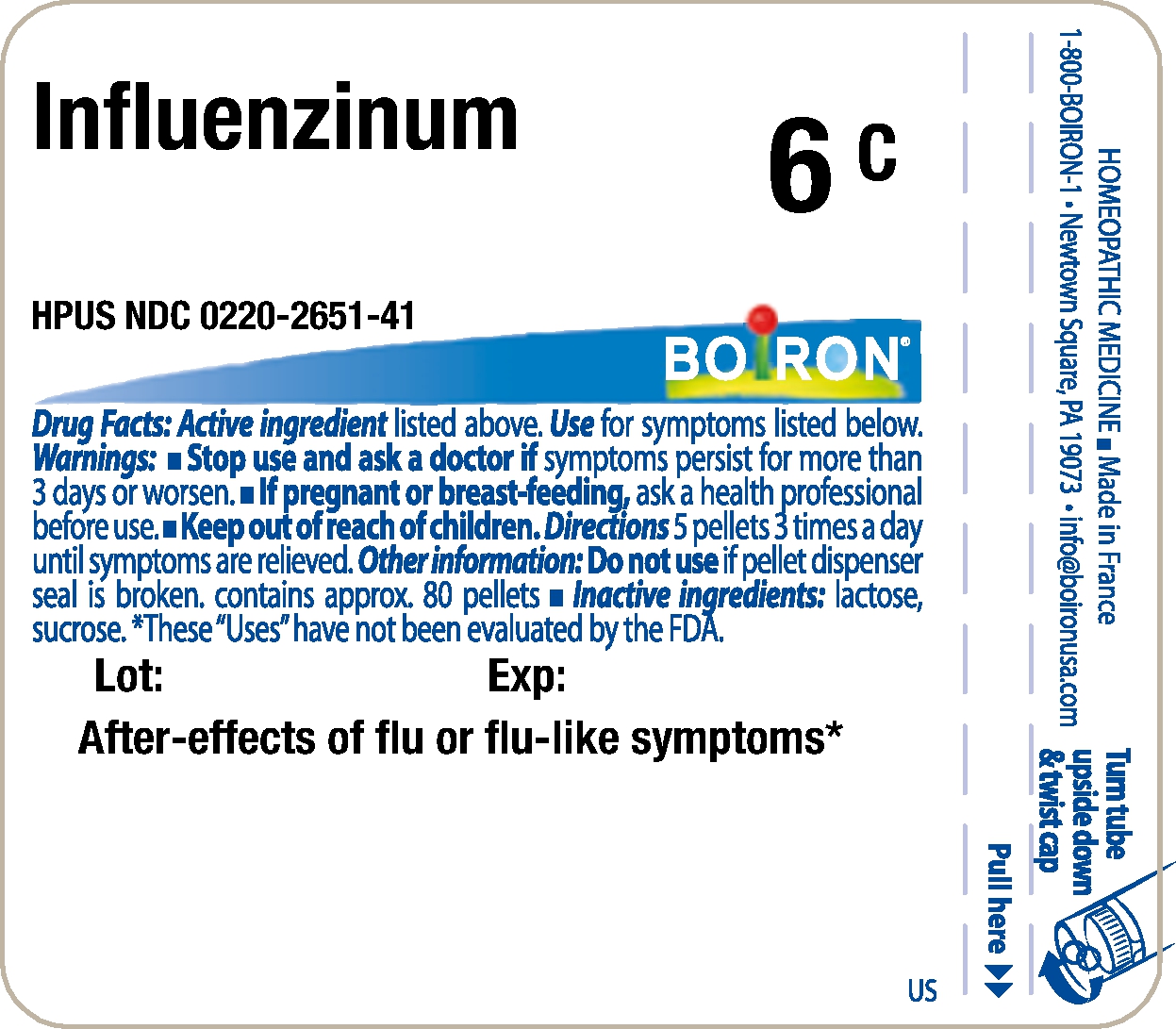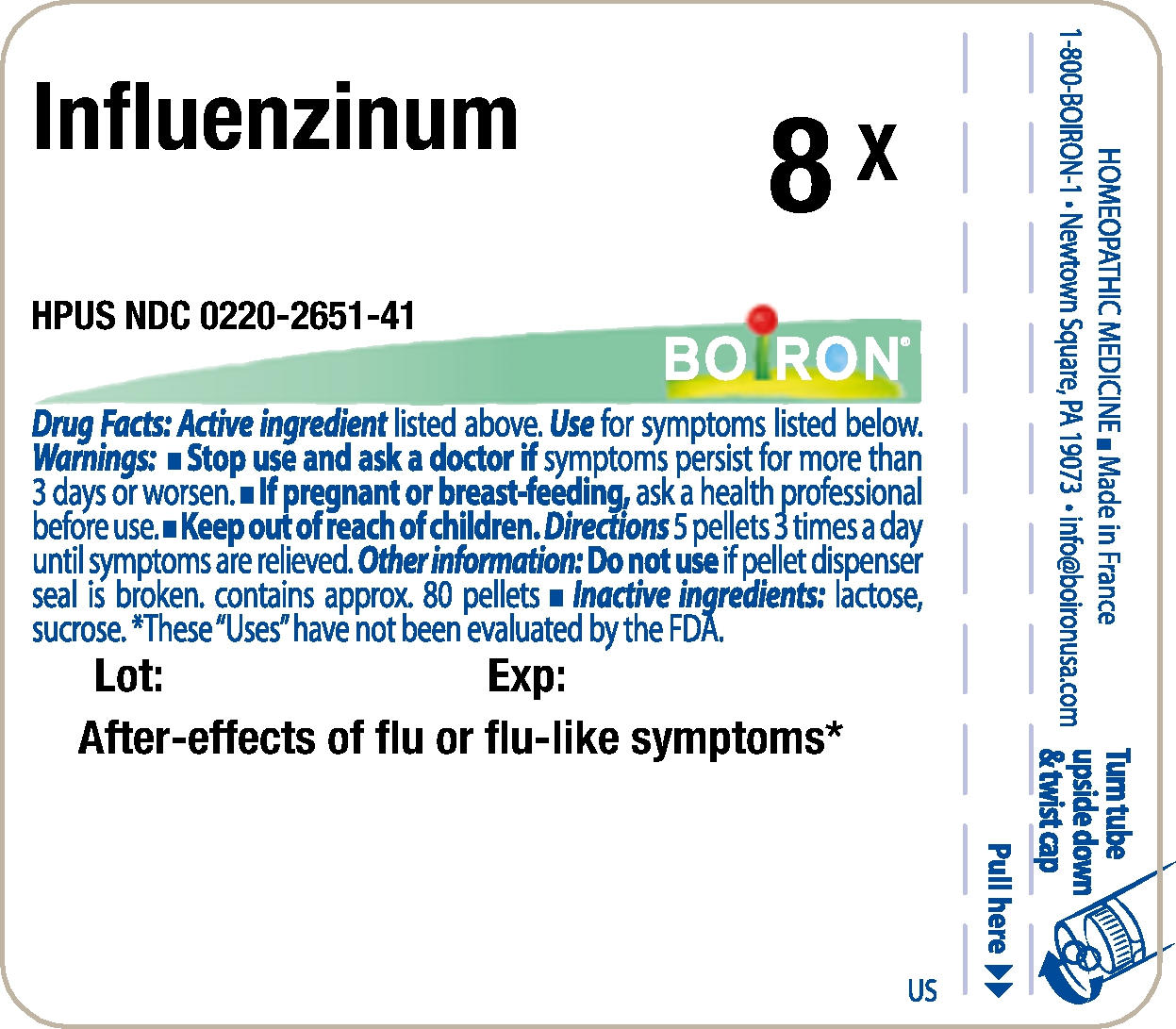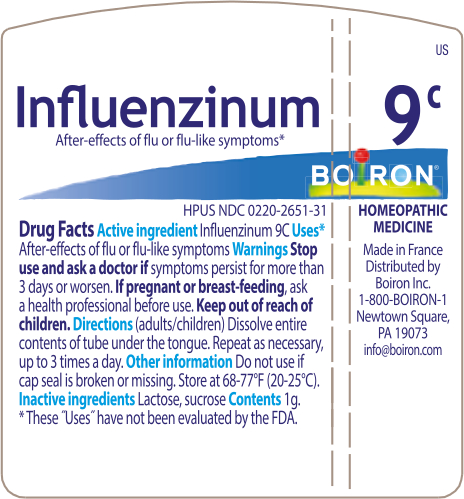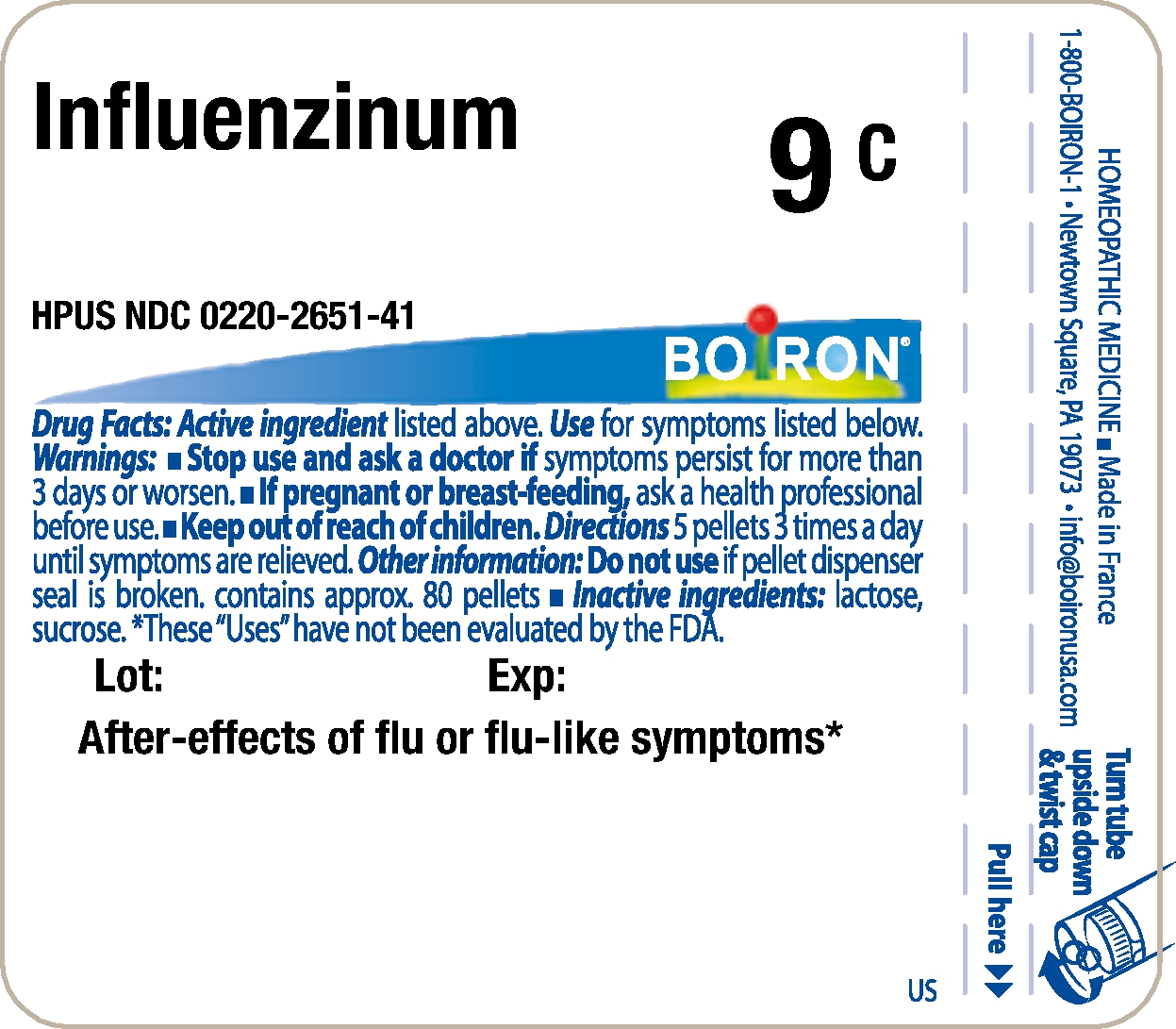 DRUG LABEL: Influenzinum
NDC: 0220-2651 | Form: PELLET
Manufacturer: Laboratoires Boiron
Category: homeopathic | Type: VACCINE LABEL
Date: 20171214

ACTIVE INGREDIENTS: INFLUENZA A VIRUS A/MICHIGAN/45/2015 X-275 (H1N1) HEMAGGLUTININ ANTIGEN (FORMALDEHYDE INACTIVATED) 8 [hp_X]/1 1; INFLUENZA A VIRUS A/HONG KONG/4801/2014 X-263B (H3N2) HEMAGGLUTININ ANTIGEN (FORMALDEHYDE INACTIVATED) 8 [hp_X]/1 1; INFLUENZA B VIRUS B/BRISBANE/60/2008 HEMAGGLUTININ ANTIGEN (FORMALDEHYDE INACTIVATED) 8 [hp_X]/1 1
INACTIVE INGREDIENTS: SUCROSE; LACTOSE

Influenzinum

Active Ingredients

Influenzinum HPUS
8X, 30X, 6C, 9C, 12C, 15C, 30C, 200CK

Use

After-effects of flu or flu-like symptoms*

Warnings

Stop use and ask a doctor if

symptoms persist for more than 3 days or worsen.

If pregnant or breast-feeding,

ask a health professional before use.

Directions

5 pellets 3 times a day until symptoms are relieved.

Other information

Do not use if pellet dispenser seal is broken.
contains approx. 80 pellets

Inactive ingredients

lactose, sucrose

Questions, Comments?

1-800-BOIRON-1
Newtown Square, PA 19073-3267
info@boironusa.com

*

These "Uses" have not been evaluated by the FDA.